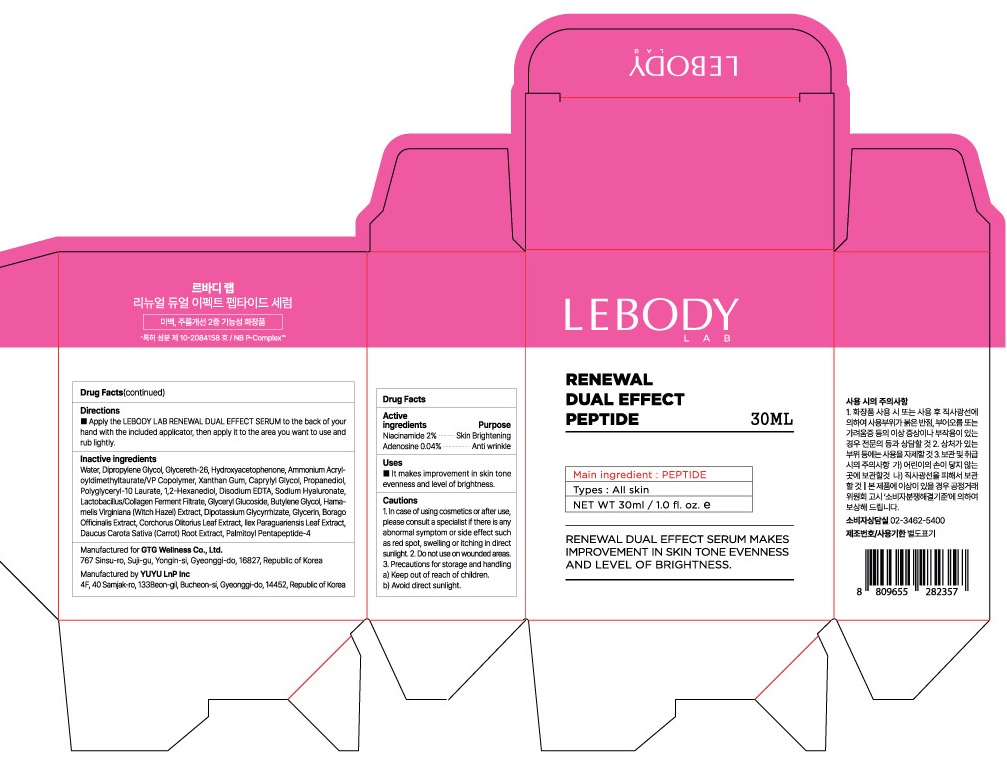 DRUG LABEL: LEBODY LAB RENEWAL DUAL EFFECT PEPTIDE SERUM
NDC: 71080-0009 | Form: LIQUID
Manufacturer: GTG Wellness Co., Ltd.
Category: otc | Type: HUMAN OTC DRUG LABEL
Date: 20230224

ACTIVE INGREDIENTS: Niacinamide 0.6 g/30 mL
INACTIVE INGREDIENTS: Water; Glycerin

ACTIVE INGREDIENTS

Niacinamide 2%

Adenosine 0.04%

INACTIVE INGREDIENTS

Water, Dipropylene Glycol, Glycereth-26, Hydroxyacetophenone, Ammonium Acryloyldimethyltaurate/VP Copolymer, Xanthan Gum, Caprylyl Glycol, Propanediol, Polyglyceryl-10 Laurate, 1,2-Hexanediol, Disodium EDTA, Sodium Hyaluronate, Lactobacillus/Collagen Ferment Filtrate, Glyceryl Glucoside, Butylene Glycol, Hamamelis Virginiana (Witch Hazel) Extract, Dipotassium Glycyrrhizate, Glycerin, Borago Officinalis Extract, Corchorus Olitorius Leaf Extract, Ilex Paraguariensis Leaf Extract, Daucus Carota Sativa (Carrot) Root Extract, Palmitoyl Pentapeptide-4

PURPOSE

Skin Brightening

Anti wrinkle

Cautions

1. In case of using cosmetics or after use, please consult a specialist if there is any abnormal symptom or side effect such as red spot, swelling or itching in direct sunlight.
2. Do not use on wounded areas.
3. Precautions for storage and handling
a) Keep out of reach of children.
b) Avoid direct sunlight.

KEEP OUT OF REACH OF CHILDREN

Uses

■ It makes improvement in skin tone evenness and level of brightness.

Directions

Apply the LEBODY LAB RENEWAL DUAL EFFECT PEPTIDE SERUM to the back of your hand with the included applicator, then apply it to the area you want to use and rub lightly.